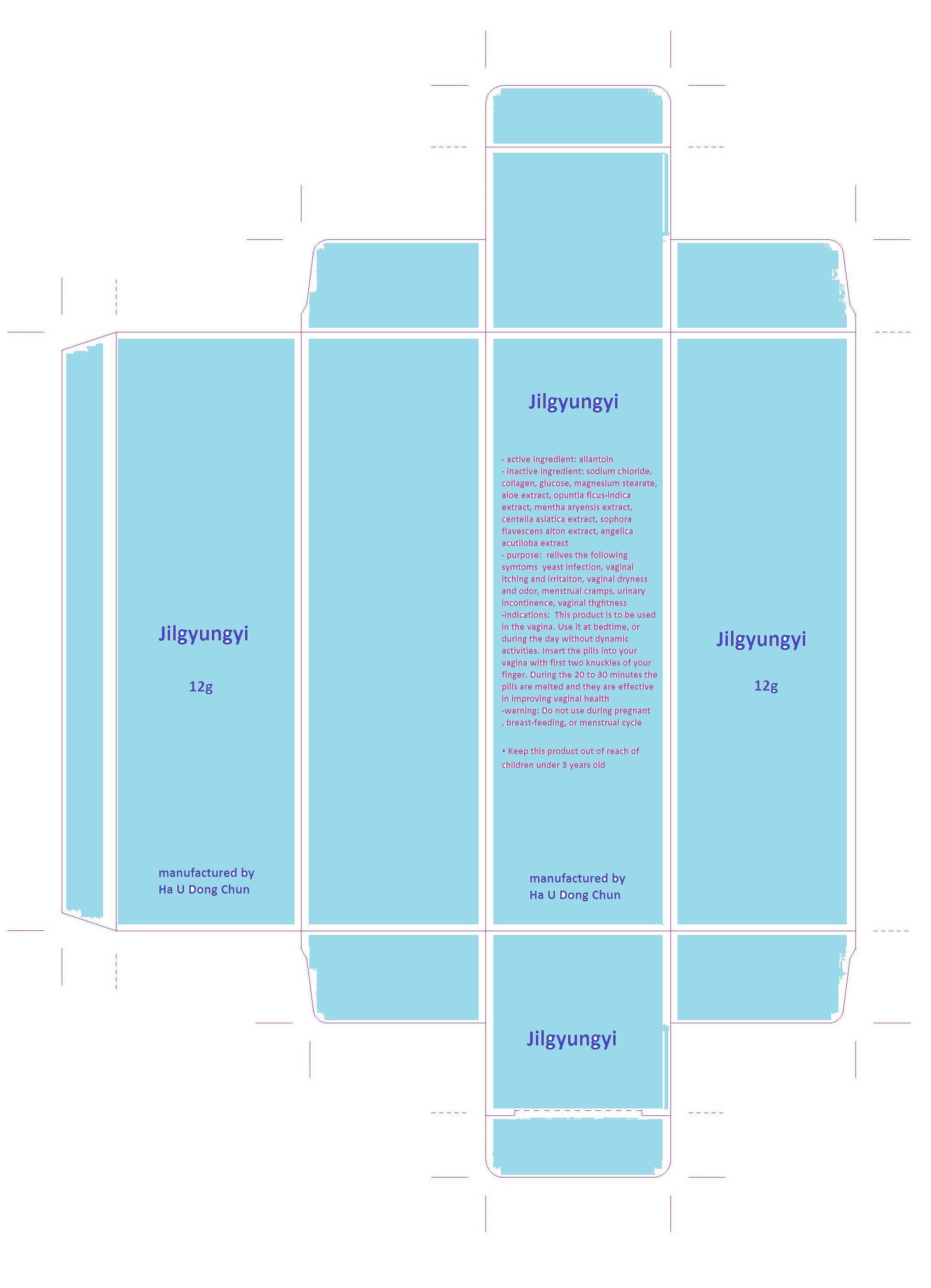 DRUG LABEL: Jilgyungyi
                
NDC: 55618-1001 | Form: TABLET
Manufacturer: HA U DONG CHUN
Category: otc | Type: HUMAN OTC DRUG LABEL
Date: 20130611

ACTIVE INGREDIENTS: ALLANTOIN 0.2 1/1 1
INACTIVE INGREDIENTS: SODIUM CHLORIDE; COLLAGENASE CLOSTRIDIUM HISTOLYTICUM; DEXTROSE; MAGNESIUM STEARATE; ALOE; OPUNTIA FICUS-INDICA; MENTHA ARVENSIS FLOWER OIL; CENTELLA ASIATICA; SOPHORA FLAVESCENS ROOT; ANGELICA ACUTILOBA ROOT OIL

Drug Facts

ACTIVE INGREDIENT

allantoin

INACTIVE INGREDIENT

sodium chloride, collagen, glucose, magnesium stearate, aloe extract, opuntia ficus-indica extract, mentha aryensis extract, centella asiatica extract, sophora flavescens aiton extract, angelica acutiloba extract

PURPOSE

- relives the following symtoms
yeast infection, vaginal itching and irritaiton, vaginal dryness and odor, menstrual cramps, urinary incontinence, vaginal thghtness

keep out of reach of the children

INDICATIONS AND USAGE

This product is to be used in the vagina. Use it at bedtime, or during the day without dynamic activities. Insert the pills into your vagina with first two knuckles of your finger. During the 20 to 30 minutes the pills are melted and they are effective in improving vaginal health

• Do not use during pregnant, breast-feeding, or menstrual cycle
• Keep this product out of reach of children under 3 years old

DOSAGE AND ADMINISTRATION

for vaginal use only